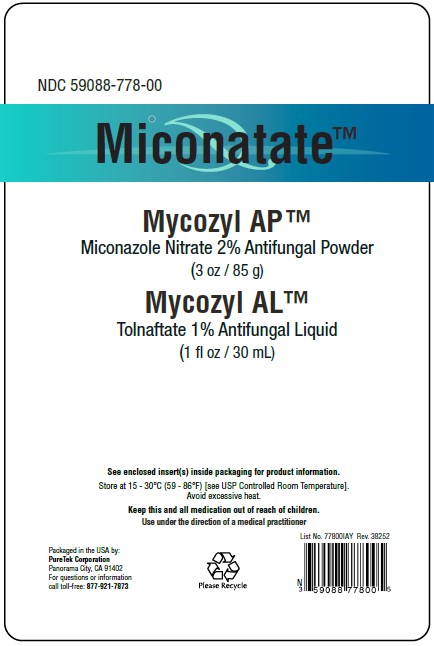 DRUG LABEL: Miconatate
NDC: 59088-778 | Form: KIT | Route: TOPICAL
Manufacturer: PureTek Corporation
Category: otc | Type: HUMAN OTC DRUG LABEL
Date: 20241016

ACTIVE INGREDIENTS: TOLNAFTATE 0.3 g/30 mL; MICONAZOLE NITRATE 2 g/85 g
INACTIVE INGREDIENTS: TEA TREE OIL; GLYCERIN; APPLE CIDER VINEGAR; LAURETH-4; BENZYL ALCOHOL; .ALPHA.-TOCOPHEROL ACETATE, DL-; DIMETHYL SULFOXIDE; EUCALYPTUS OIL; LAVENDER OIL; POLYETHYLENE GLYCOL 400; ARGAN OIL; LEVOMENOL; CARTHAMUS TINCTORIUS (SAFFLOWER) OLEOSOMES; SODIUM BENZOATE; GINGER; CANANGA ODORATA FLOWER; XYLITOL; SILICON DIOXIDE; ALOE VERA LEAF; NYLON-12; STARCH, CORN; KUKUI NUT OIL; HYALURONATE SODIUM

Miconatate™
Kit
Mycozyl AP™, Miconazole Nitrate 2%, Antifungal Powder (3 oz / 85 g)
Mycozyl AL™, Tolnaftate 1%, Antifungal Liquid (1 fl oz / 30 mL)

Active ingredient

Miconazole Nitrate 2%

Purpose

Antifungal

Uses

- for the treatment of most athlete's foot (tinea pedis), jock itch (tinea cruris), ringworm (tinea corporis).
- relieves itching, burning, cracking, scaling, and discomfort which accompany these conditions.

Warnings

For external use only.

Do not use on

- children under 2 years of age unless directed by a doctor

When using this product

- do not get into eyes

Stop use and ask a doctor if

- for athlete's foot and ringworm - irritation occurs or there is no improvement within 4 weeks
- for jock itch - irritation occurs or there is no improvement within 2 weeks

Keep out of reach of children.

If swallowed, get medical help or contact a Poison Control Center right away.

Directions

- clean the affected area and dry thoroughly
- apply a thin layer of the product over affected area twice daily (morning and night) or as directed by a doctor
- supervise children in the use of this product
- for athlete's foot, pay special attention to spaces between the toes, wear well-fitting, ventilated shoes, and change shoes and socks at least once daily
- for athlete's foot and ringworm, use daily for 4 weeks
- for jock itch, use daily for 2 weeks
- if condition persists longer, consult a doctor. This product is not effective on the scalp or nails.

Other information

- protect from freezing
- avoid excessive heat
- do not use if package is damaged

Inactive ingredients

Aleurites Moluccana (Kukui) Seed Oil, Aloe Barbadensis (Aloe Vera) Leaf Juice Powder, Bisabolol, Carthamus Tinctorius (Safflower) Oleosomes, Fragrance, Nylon-12, Silica, Sodium Benzoate, Sodium Hyaluronate, Zea Mays (Corn) Starch, Zingiber Officinale (Ginger) Root Extract.

Active ingredient

Tolnaftate 1%

Purpose

Antifungal

Uses

- for the treatment of most athlete's foot (tinea pedis) and ringworm (tinea corporis).
- relieves itching, burning, cracking, scaling, and discomfort which accompany these conditions.
- for the prevention of most Athlete’s foot with daily use.
- eliminates fungus on fingers, toes, and around the nails.
- eliminates and helps stop the spread of fungal infections on cuticles around nail edges and under the nail tips where reachable with applicator brush.

Warnings

For external use only

Do not use on

children under 2 years of age unless directed by a doctor.

When using this product

- do not get into eyes

Stop use and ask a doctor

- for athlete's foot and ringworm - if irritation occurs or there is no improvement within 4 weeks
- for prevention of athlete’s foot - if irritation occurs, discontinue use and consult a doctor

Keep out of reach of children.

If swallowed, get medical help or contact a Poison Control Center right away.

Directions

- clean the affected area and dry thoroughly
- apply a thin layer of the product over affected area twice daily (morning and night) paying special attention to the edges of the nail, cuticles, and skin around the nails or as directed by a doctor
- supervise children in the use of this product
- for athlete's foot, pay special attention to spaces between the toes, wear well-fitting, ventilated shoes, and change shoes and socks at least once daily
- for athlete's foot and ringworm, use daily for 4 weeks
- if condition persists longer, consult a doctor.

Use under the direction of a medical practitioner

Other information

- Store at 15 - 30°C (59° - 86°F) [see USP Controlled Room Temperature].
- avoid excessive heat
- do not use if package is damaged

How Supplied

Mycozyl AL™ Antifungal Liquid is supplied in a 1 fl oz / 30 mL glass bottle with a screw cap fitted with a brush applicator (NDC 59088-443-03)

Inactive ingredients

Apple Cider Vinegar, Argania Spinosa (Argan) Kernel Oil, Benzyl Alcohol, DMSO (Dimethyl Sulfoxide), Eucalyptus Globulus (Eucalyptus) Leaf Oil, Glycerin, Laureth-4, Lavandula Angustifolia (Lavender) Oil, Melaleuca Alternifolia (Tea Tree) Leaf Oil, PEG-8, DL-alpha-tocopheryl acetate.

Miconatate™

Packaged in the USA by:
PureTek Corporation
Panorama City, CA 91402
For questions or information
call toll-free: 877-921-7873